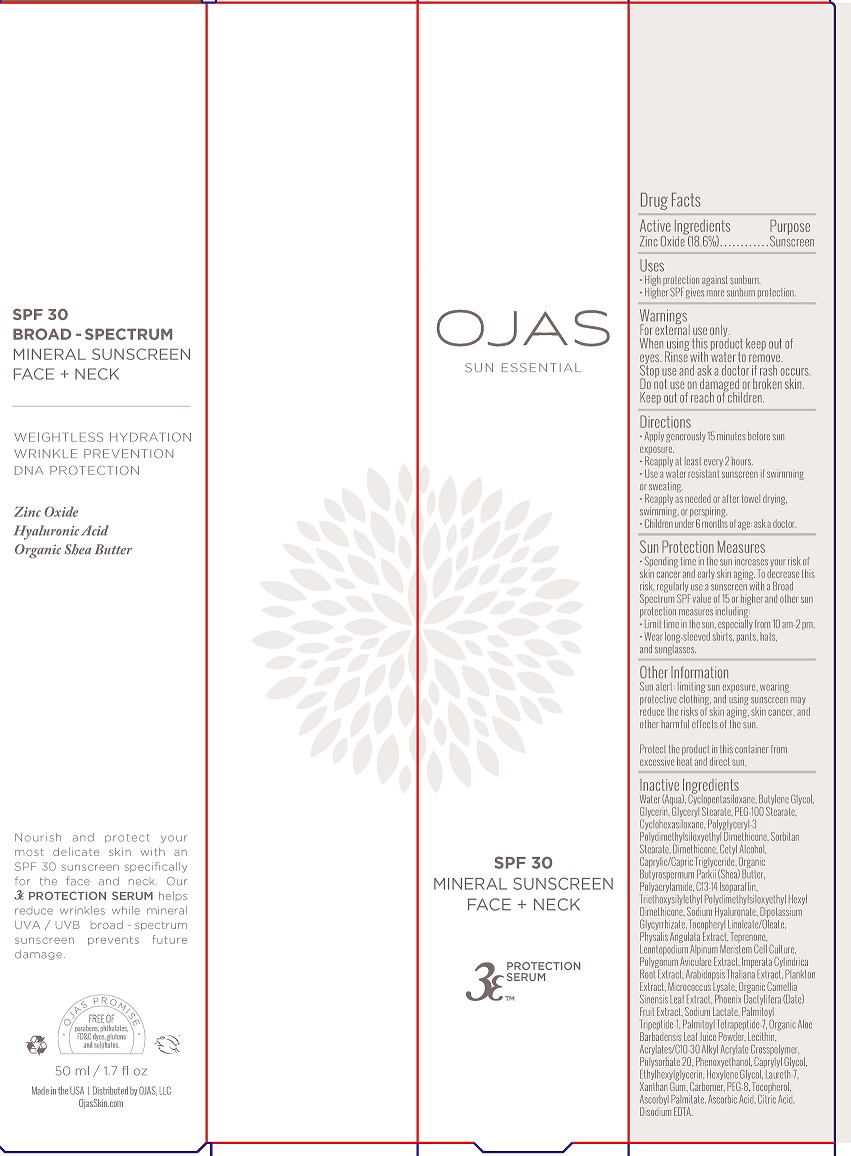 DRUG LABEL: SPF 30 MINERAL SUNSCREEN FACE  NECK
NDC: 70867-104 | Form: CREAM
Manufacturer: OJAS, LLC
Category: otc | Type: HUMAN OTC DRUG LABEL
Date: 20160729

ACTIVE INGREDIENTS: AVOBENZONE 20 mg/1 mL; OCTINOXATE 75 mg/1 mL; OCTISALATE 50 mg/1 mL; OCTOCRYLENE 15 mg/1 mL; OXYBENZONE 60 mg/1 mL
INACTIVE INGREDIENTS: WATER; ALKYL (C12-15) BENZOATE; BUTYLENE GLYCOL; OCTYLDODECYL NEOPENTANOATE; CYCLOMETHICONE 5; MEDIUM-CHAIN TRIGLYCERIDES; GLYCERIN; SORBITAN MONOOLEATE; UBIDECARENONE; PHYSALIS ANGULATA; TEPRENONE; HYALURONATE SODIUM; GREEN TEA LEAF; ACTINIDIA CHINENSIS ROOT; ARTEMISIA VULGARIS ROOT; CENTELLA ASIATICA; ECHINACEA PURPUREA; PALMITOYL PENTAPEPTIDE-4; LEONTOPODIUM ALPINUM FLOWER; ARABIDOPSIS THALIANA; ALOE VERA LEAF; POLYGONUM AVICULARE TOP; XANTHAN GUM; EGG PHOSPHOLIPIDS; CARBOMER COPOLYMER TYPE B (ALLYL PENTAERYTHRITOL CROSSLINKED); CARBOMER COPOLYMER TYPE A (ALLYL PENTAERYTHRITOL CROSSLINKED); POLYSORBATE 20; TROLAMINE; PHENOXYETHANOL; CAPRYLYL GLYCOL; ETHYLHEXYLGLYCERIN; HEXYLENE GLYCOL; POLYETHYLENE GLYCOL 400; TOCOPHEROL; ASCORBYL PALMITATE; ASCORBIC ACID; CITRIC ACID MONOHYDRATE; EDETATE DISODIUM

Active Ingredients:

ZINC OXIDE 18.6%

Purpose: Sunscreen

Uses:

- High protection against sunburn.
- Higher SPF gives more sunburn protection.

Warnings: For external use only.

When using this product keep out of eyes. Rinse with to remove.

Stop use ans ask a doctor if rash occurs.

Do not use on damaged or broken skin.

Keep out of reach of children.

Directions:

- Apply generously 15 minutes before sun exposure.
- Reapply at least every 2 hours.
- Use a water resistant sunscreen if swimming or sweating.
- Reapply as needed or after towel drying, swimming or perspiring.
- children under 6 months of age: ask a doctor.

STORAGE AND HANDLING

Protect the product in in this container from excessive heat and direct sun.

INACTIVE INGREDIENTS

Water (Aqua), Cycclopentasiloxane, Butylene Glycol, Glycerin, Glyceryl Stearate, PEG-100 Stearate, Cyclohexasiloxane, Polyglyceryl-3 Polydimethylsiloxyethyl Dimethicone, Sorbitan Stearate, Dimethicone, Cetyl Alcohol, Caprylic/Capric Triglyceride, Organic Butyrospermum Parkii (Shea) Butter, Polyaqcrylamide, C13-14 Isoparaffin, Triethoxysilylethyl Polydimethylsiloxyethyl Hexyl Dimethicone, Sodium Hyaluronate, Dipotassium Glycyrrhizate, Tocopheryl Linoleate/Oleate, Physalis Angulata Extract, Teprenone, Leontopodium Alpinum Meristem Cell Culture, Polygonum Aviculare Extract, Imperata Cylindrica Root Extract, Arabidopsis Thaliana Extract, Plankton Extract, Micrococcus Lysate, Organic Camellia Sinensis Leaf Extract, Phoenix Dactylifera (Date) Fruit Extract, Sodium Lactate, Palmitoyl Tripeptide-1, Palmitoyl Tetrapeptide-7, Organic Aloe Barbadensis Leaf Juice Powder, Lecithin, Acrylates/C10-30 Alkyl Acrylate Crosspolymer, Polysorbate 20, Phenoxyethanol, Caprylyl Glycol, Ethylhexylglycerin, Hexylene Glycol, Laureth-7, Xanthan Gum, Carbomer, PEG-8, Tocopherol, Ascorbyl Palmitate, Ascorbic Acid, Citric Acid, Disodium EDTA.